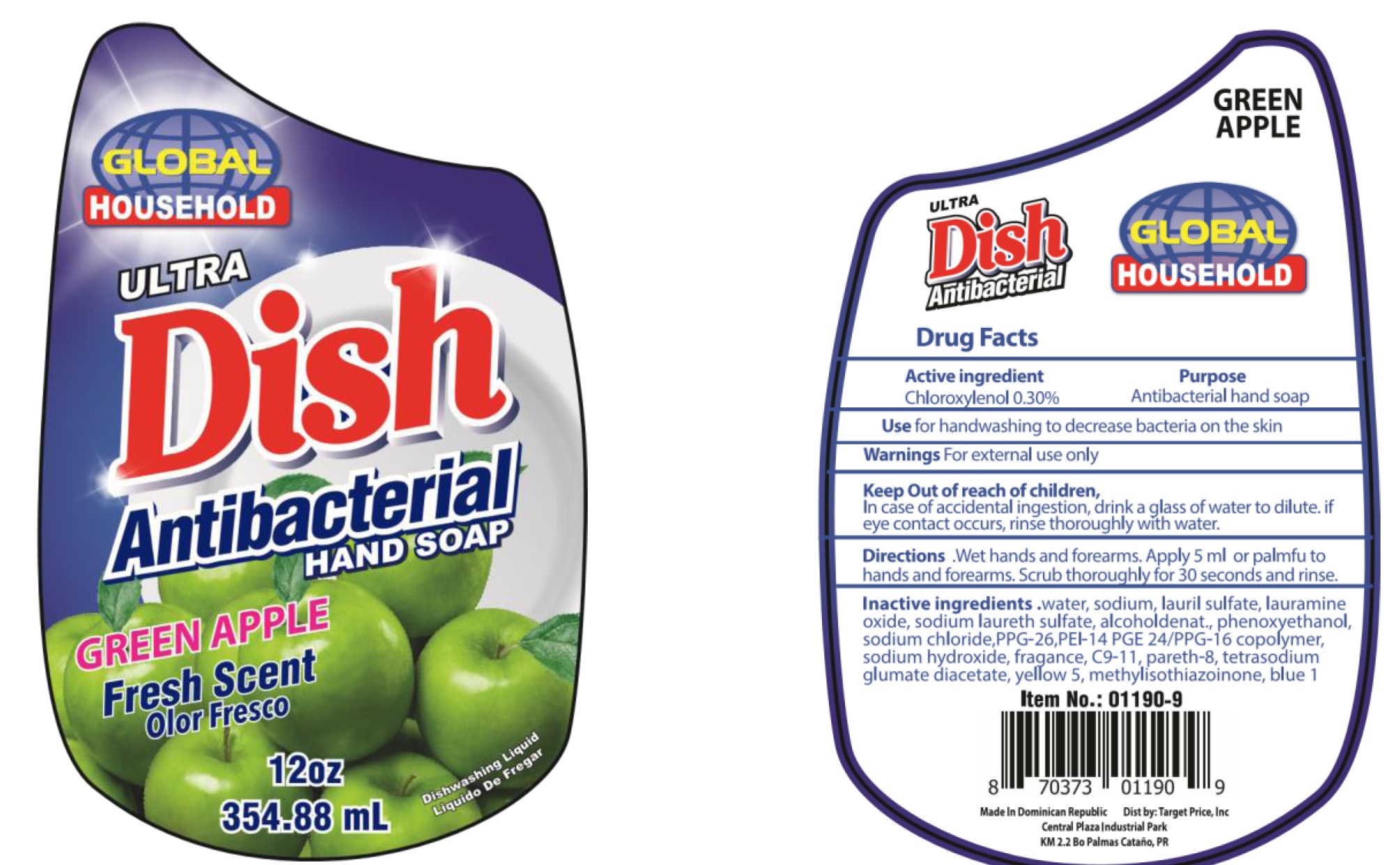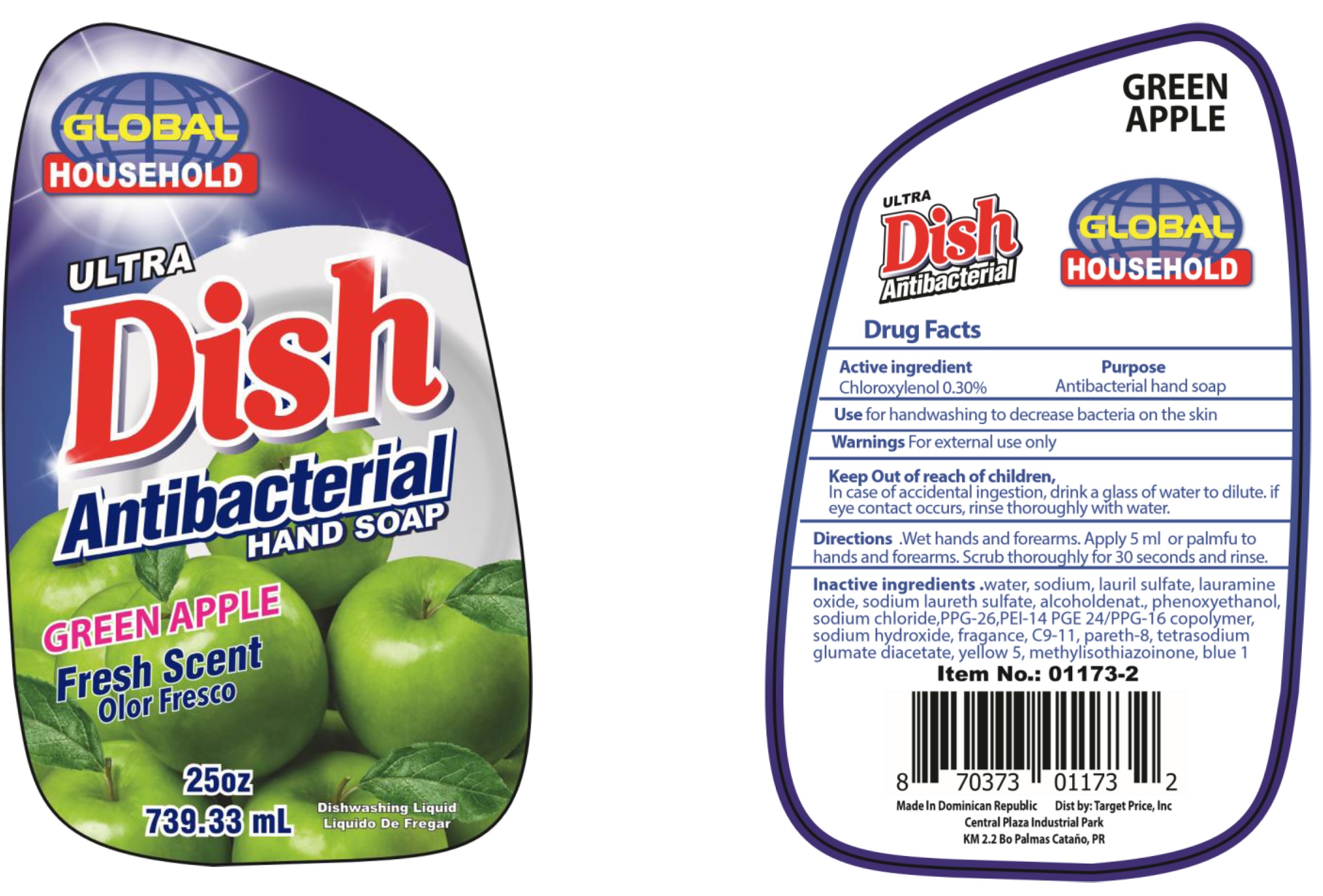 DRUG LABEL: Global Household  Antibacterial Green Apple Fresh Scent
NDC: 72146-044 | Form: LIQUID
Manufacturer: TARGET PRICE, INC.
Category: otc | Type: HUMAN OTC DRUG LABEL
Date: 20200904

ACTIVE INGREDIENTS: CHLOROXYLENOL 3 mg/1 mL
INACTIVE INGREDIENTS: WATER; SODIUM; LAURYL SULFATE; LAURAMINE OXIDE; SODIUM LAURETH SULFATE; ALCOHOL; PHENOXYETHANOL; SODIUM CHLORIDE; PPG-26; SODIUM HYDROXIDE; C9-11 PARETH-8; FD&C YELLOW NO. 5; METHYLISOTHIAZOLINONE; FD&C BLUE NO. 1

Global Household Antibacterial Green Apple Fresh Scent

Active ingredient

Chloroxylenol 0.30%

Purpose

Antibacterial hand soap

Use

for handwashing to decrease bacteria on the skin

Warnings

For external use only

Keep Out of reach of children.

In case of accidental ingestion, drink a glass of water to dilute. if eye contact occurs, rinse thoroughly with water.

Directions.

Wet hands and forearms. Apply 5 ml or palmfu to hands and forearms. Scrub thoroughly for 30 seconds and rinse.

Inactive ingredients.

water, sodium, lauril sulfate, lauramine oxide, sodium laureth sulfate, alcoholdenat., phenoxyethanol, sodium chloride, PPG-26, PEI-14 PGE24/PPG-16 copolymer, sodium hydroxide, fragrance, C9-11, pareth-8, tetrasodium glumate diacetate, yellow 5, methylisothiazoinone, blue 1